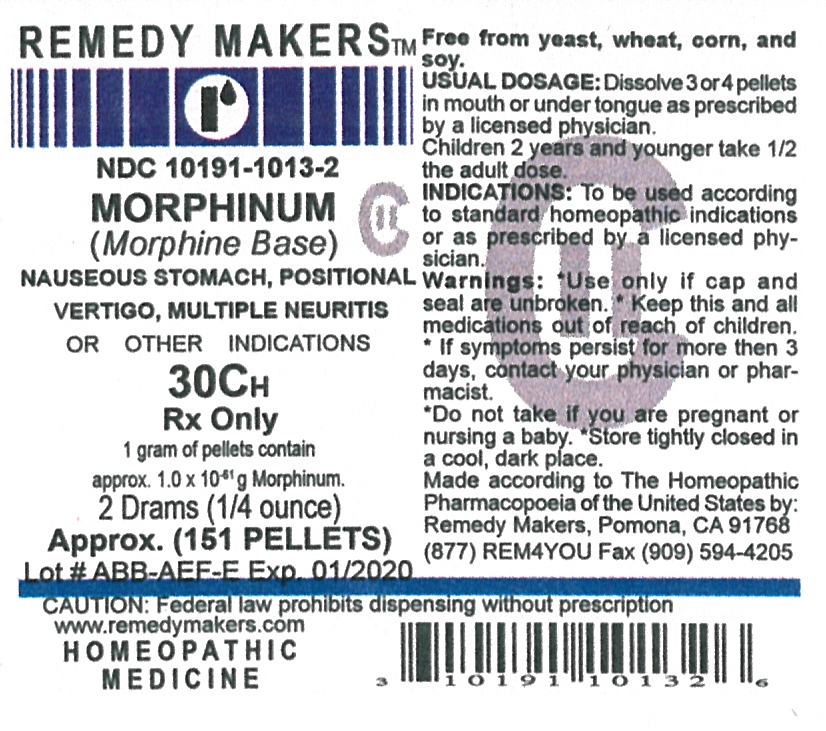 DRUG LABEL: MORPHINUM
NDC: 10191-1013 | Form: PELLET
Manufacturer: Remedy Makers
Category: homeopathic | Type: HUMAN PRESCRIPTION DRUG LABEL
Date: 20110314
DEA Schedule: CII

ACTIVE INGREDIENTS: MORPHINE 30 [hp_C]/1 1
INACTIVE INGREDIENTS: SUCROSE; LACTOSE

MORPHINUM 30C (Morphine Base) Rx Only

CONTROLLED SUBSTANCE

Morphine Base

INDICATIONS AND USAGE

NAUSEOUS STOMACH, POSITIONAL VERTIGO, MULTIPLE NEURITIS, OR OTHER INDICATIONS.

WARNINGS

WARNING:Keep this and all medications out of reach of children.

INDICATIONS AND USAGE

INDICATIONS: To be use according to standard homeopathic indications,or as prescribed by a licensed physician.

Free from yeast, wheat, corn, and soy.

WARNINGS

WARNING SECTION: Use only if cap and seal are unbroken. If symptoms persist for more than 3 days, contact your physician or pharmacist. Do not take if you are pregnant or nursing a baby. Store tightly closed in a cool, dark place. Made according to The Homeopathic Pharmacopoeia of the United State by: Remedy Makers, Pomona, CA 91768

DOSAGE AND ADMINISTRATION

USUAL DOSAGE: Dissolve 3 or 4 pellets in mouth or tongue as prescribed by a licensed physician. Children 2 years and younger take 1/2 the adult dose

INACTIVE INGREDIENT

80% SUCROSE / 20% LACTOSE